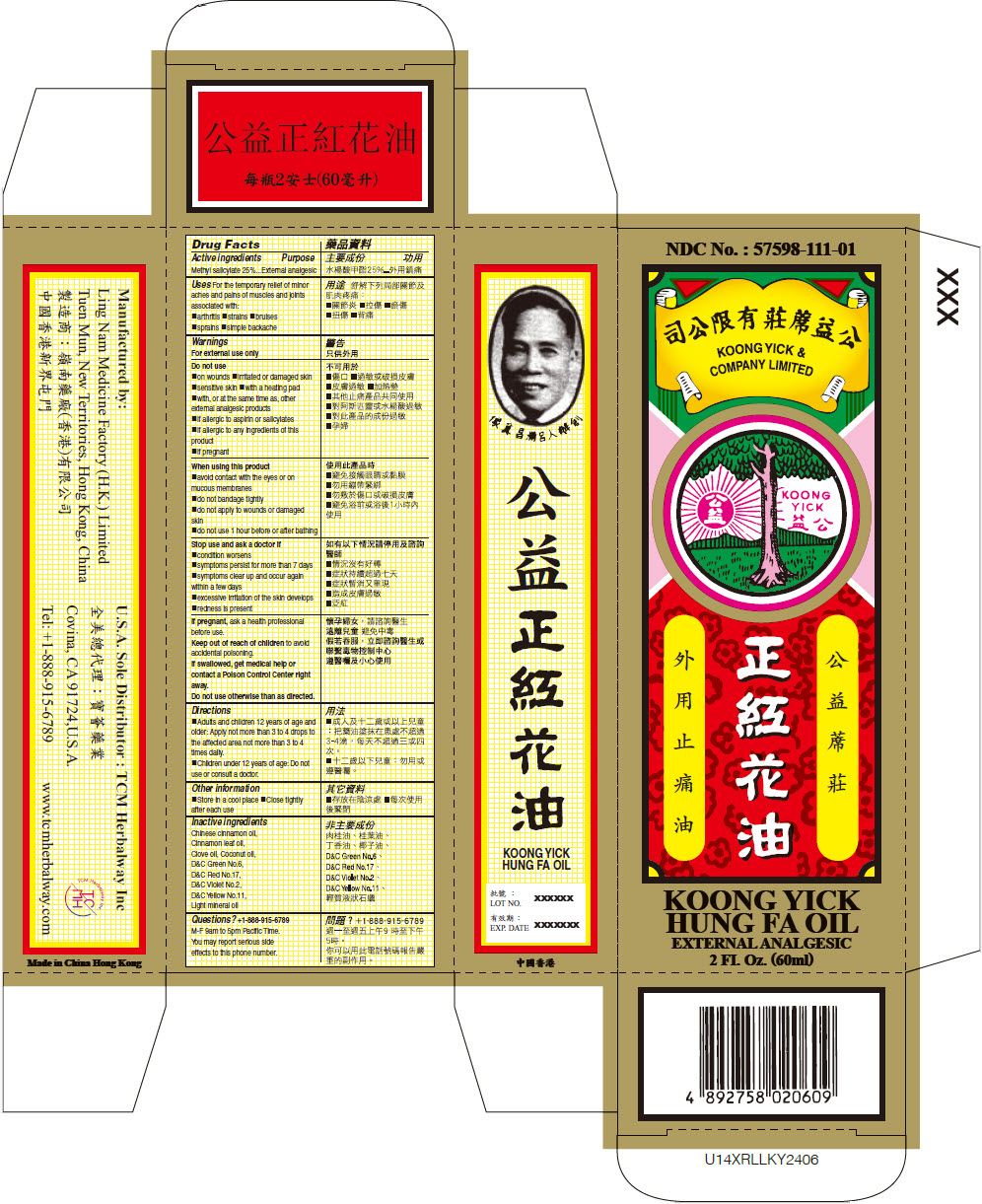 DRUG LABEL: Koong Yick Hung Fa
NDC: 57598-111 | Form: OIL
Manufacturer: Ling Nam Medicine Factory (H.K.) Ltd.
Category: otc | Type: HUMAN OTC DRUG LABEL
Date: 20240718

ACTIVE INGREDIENTS: METHYL SALICYLATE 25 g/100 mL
INACTIVE INGREDIENTS: CHINESE CINNAMON OIL; CINNAMON LEAF OIL; CLOVE OIL; COCONUT OIL; LIGHT MINERAL OIL; D&C RED NO. 17; D&C YELLOW NO. 11; D&C VIOLET NO. 2; D&C GREEN NO. 6

Koong Yick Hung Fa Oil

Drug Facts

ACTIVE INGREDIENT

Active Ingredients | Purpose
Methyl salicylate 25% | External analgesic

Uses

For temporary relief of minor aches and pains of muscles and joints due to:

- arthritis
- strains
- bruises
- sprains
- simple backache

Warnings

For external use only

Do not use

- on wounds
- irritated or damaged skin
- sensitive skin
- with a heating pad
- with, or at the same time as, other external analgesic products
- if allergic to aspirin or salicylates
- if allergic to any ingredients of this product
- if pregnant

When using this product

- avoid contact with the eyes or on mucous membranes
- do not bandage tightly
- do not apply to wounds or damaged skin
- do not use 1 hour before or after bathing

Stop use and ask a doctor if

- condition worsens
- symptoms persist for more than 7 days
- symptoms clear up and occur again within a few days
- excessive irritation of the skin develops
- redness is present

PREGNANCY OR BREAST FEEDING

If pregnant, ask health professional before use.

Keep out of reach of children to avoid accidental poisoning.

If swallowed, get medical help or contact a Poison Control Center right away.

Do not use otherwise than as directed.

Directions

- Adults and children 12 years of age and older: Apply not more than 3 to 4 drops to the affected area not more than 3 to 4 times daily.
- Children under 12 years of age: Do not use or consult a doctor.

Other information

- Store in a cool place
- Close tightly after each use

Inactive ingredients

Chinese cinnamon oil, Cinnamon leaf oil, Clove oil, Coconut oil, D&C Green No.6, D&C Red No.17, D&C Violet No.2, D&C Yellow No.11, Light mineral oil

Questions?

+1-888-915-6789

M-F 9am to 5pm Pacific Time.

You may report serious side effects to this phone number.

Manufactured by:
Ling Nam Medicine Factory (H.K.) Limited
Tuen Mun, New Territories, Hong Kong, China

PRINCIPAL DISPLAY PANEL - 60 ml Bottle Box

NDC No. : 57598-111-01

KOONG YICK &
COMPANY LIMITED

KOONG
YICK

KOONG YICK
HUNG FA OIL

EXTERNAL ANALGESIC

2 FI. Oz. (60ml)